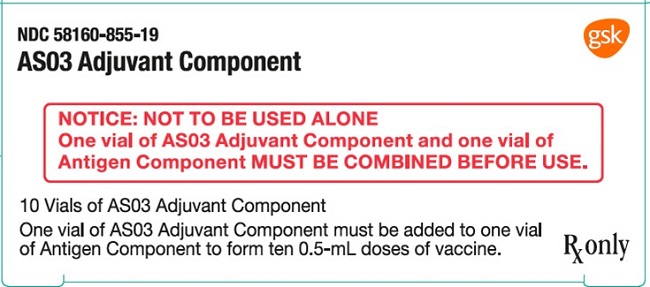 DRUG LABEL: AS03
NDC: 58160-855 | Form: INJECTION, SOLUTION
Manufacturer: GlaxoSmithKline Biologicals SA
Category: other | Type: VACCINE LABEL
Date: 20251231

SPL UNCLASSIFIED SECTION

Health Care Professional and Patient Fact Sheets are not available at this time.

PRINCIPAL DISPLAY PANEL

NDC 58160-855-19

AS03 Adjuvant Component

NOTICE: NOT TO BE USED ALONE

One vial of AS03 Adjuvant Component and one vial of Antigen Component MUST BE COMBINED BEFORE USE.

10 Vials of AS03 Adjuvant Component

One vial of AS03 Adjuvant Component must be added to one vial of Antigen Component to form ten 0.5-mL doses of vaccine.

Rx only

Rev. 11/20

504407